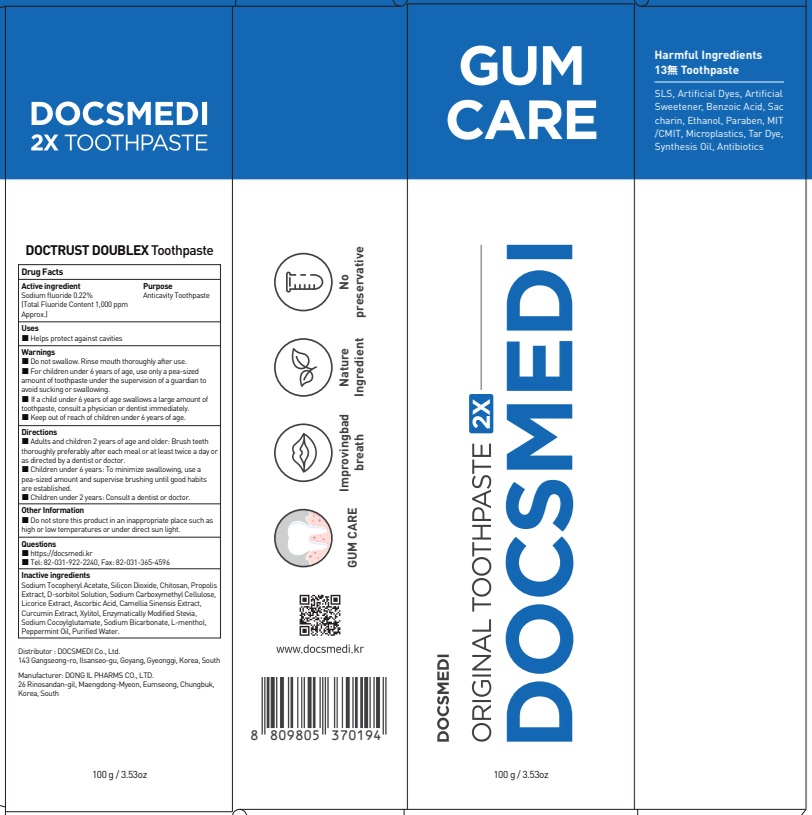 DRUG LABEL: DOCTRUST DOUBLEX Tooth
NDC: 73242-1122 | Form: PASTE, DENTIFRICE
Manufacturer: DONG IL PHARMS CO.,LTD
Category: otc | Type: HUMAN OTC DRUG LABEL
Date: 20251125

ACTIVE INGREDIENTS: SODIUM FLUORIDE 0.22 g/100 g
INACTIVE INGREDIENTS: SILICON DIOXIDE; PROPOLIS WAX

ACTIVE INGREDIENT

Sodium fluoride 0.22%
(Total Fluoride Content 1,000 ppm Approx.)

INACTIVE INGREDIENTS

Sodium Tocopheryl Acetate, Silicon Dioxide, Chitosan, Propolis Extract, D-sorbitol Solution, Sodium Carboxymethyl Cellulose, Licorice Extract, Ascorbic Acid, Camellia Sinensis Extract, Curcumin Extract, Xylitol, Enzymatically Modified Stevia, Sodium Cocoylglutamate, Sodium Bicarbonate, L-menthol, Peppermint Oil, Purified Water

PURPOSE

Anticavity Toothpaste

WARNINGS

■ Do not swallow. Rinse mouth thoroughly after use.

■ For children under 6 years of age, use only a pea-sized amount of toothpaste under the supervision of a guardian to avoid sucking or swallowing.

■ If a child under 6 years of age swallows a large amount of toothpaste, consult a physician or dentist immediately.

■ Keep out of reach of children under 6 years of age.

KEEP OUT OF REACH OF CHILDREN

■ Keep out of the reach of children under 6 years of age.

Uses

■ Helps protect against cavities

Directions

■ Adults and children 2 years of age and older: Brush teeth thoroughly preferably after each meal or at least twice a day or as directed by a dentist or doctor.
■ Children under 6 years: To minimize swallowing, use a pea-sized amount and supervise brushing until good habits are established.
■ Children under 2 years: Consult a dentist or doctor.

Other Information

■ Do not store this product in an inappropriate place such as high or low temperatures or under direct sun light

Questions

■ https://docsmedi.kr

■ Tel: 82-031-922-2240, Fax: 82-031-365-4596